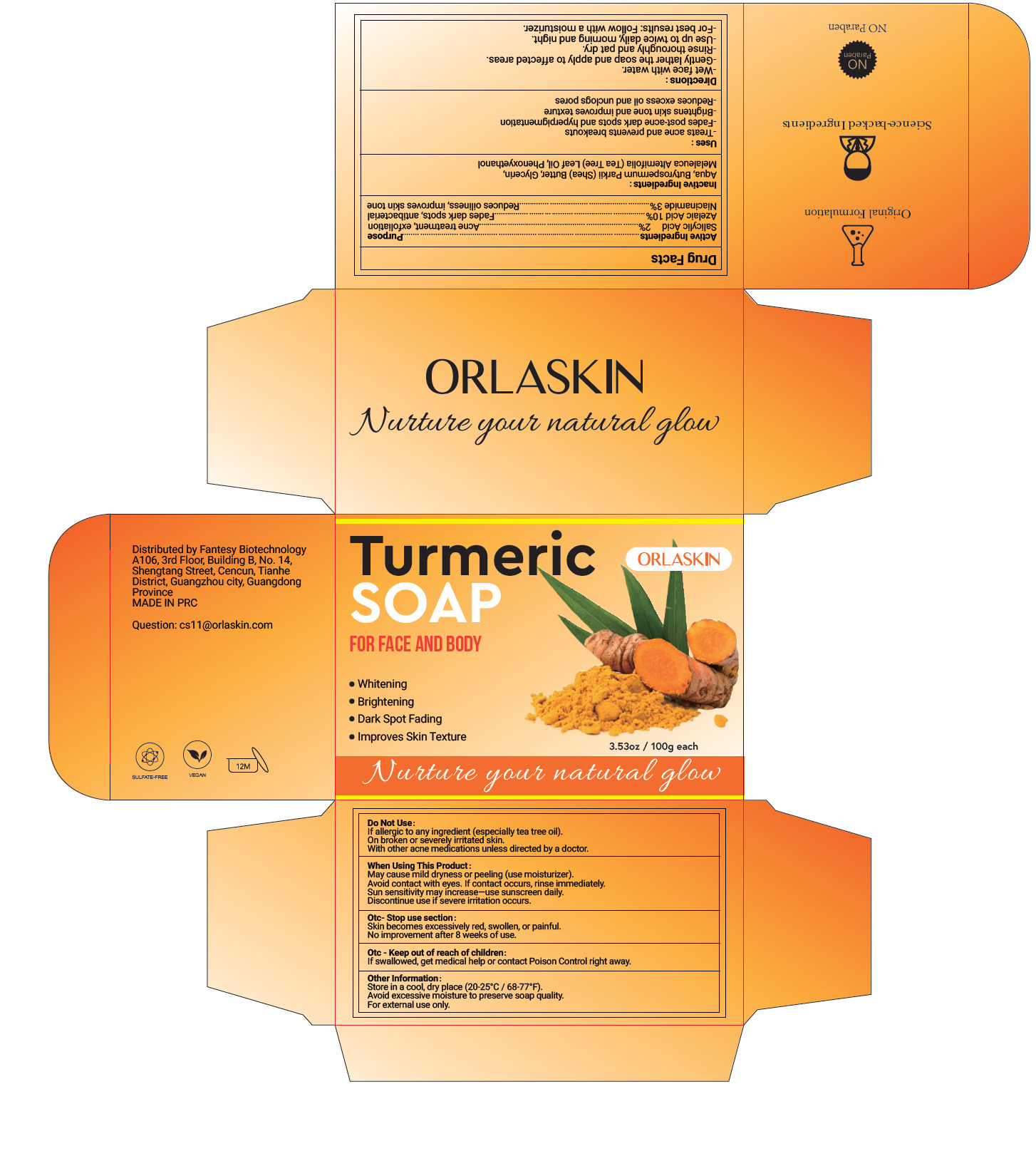 DRUG LABEL: whitening
NDC: 84356-002 | Form: SOAP
Manufacturer: Guangzhou Yapeng Refinement Chemical Co., Ltd.
Category: otc | Type: HUMAN OTC DRUG LABEL
Date: 20250616

ACTIVE INGREDIENTS: NIACINAMIDE 3 g/100 g; SALICYLIC ACID 2 g/100 g; AZELAIC ACID 10 g/100 g
INACTIVE INGREDIENTS: GLYCERIN; BUTYROSPERMUM PARKII (SHEA) BUTTER; AQUA; PHENOXYETHANOL; MELALEUCA ALTERNIFOLIA (TEA TREE) LEAF OIL

84356-002

Active Ingredient(s)

Niacinamide 3%

Azelaic Acid 10%

Salicylic Acid 2%

Purpose

Acne treatment, exfoliation
Fades dark spots, antibacterial
Reduces oiliness, improves skin tone

Use

-Treats acne and prevents breakouts
-Fades post-acne dark spots and hyperpigmentation
- Brightens skin tone and improves texture
-Reduces excess oil and unclogs pores

Warnings

If severe irritation occurs, please stop using immediately

Do not use

If allergic to any ingredient (especially tea tree oil).
On broken or severely irritated skin.
With other acne medications unless directed by a doctor

WHEN USING

May cause mild dryness or peeling (use moisturizer).
Avoid contact with eyes. If contact occurs, rinse immediately.
Sun sensitivity may increase—use sunscreen daily.
Discontinue use if severe irritation occurs.

STOP USE

Skin becomes excessively red, swollen, or painful.
No improvement after 8 weeks of use.

KEEP OUT OF REACH OF CHILDREN

If swallowed, get medical help or contact Poison Control right away.

Directions

-Wet face with water.
-Gently lather the soap and apply to affected areas.
-Rinse thoroughly and pat dry.
-Use up to twice daily, morning and night.
-For best results: Follow with a moisturizer.

Other information

Store in a cool, dry place (20-25°C / 68-77°F).
Avoid excessive moisture to preserve soap quality.
For external use only.

Inactive ingredients

Aqua, Butyrospermum Parkii (Shea) Butter, Glycerin, Melaleuca Alternifolia (Tea Tree) Leaf Oil, Phenoxyethanol